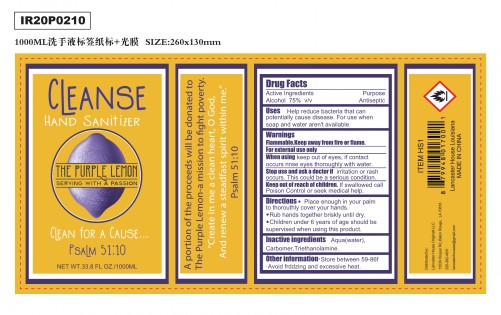 DRUG LABEL: Hand Sanitizer
NDC: 74440-005 | Form: GEL
Manufacturer: Jiangxi Iris Chemical Co.,Ltd
Category: otc | Type: HUMAN OTC DRUG LABEL
Date: 20200515

ACTIVE INGREDIENTS: ALCOHOL 75 mL/100 mL
INACTIVE INGREDIENTS: TROLAMINE; WATER; CARBOMER HOMOPOLYMER, UNSPECIFIED TYPE

Hand Sanitizer

Active Ingredients

Alcohol 75%vlv

Purpose

Antiseptic

Uses

Help reduce bacteria that can

potentially cause disease.For use when

soap and water aren't available.

Warnings

Flammable. Keep away from fire or flame.For external use only.

When using

keep out of eyes, if contact occurs rinse eyes thoroughly with water.

Stop use and ask a doctor if

irritation or rash occurs.This could be a serious condition.

Keep out of reach of children

If swallowed call

Poison Control or seek medical help.

Directions

Place enough in your palm to thorouthly cover your hands.

Rub hands together briskly until dry.

Children under 6 years of age should be supervised when using this product.

Other information

Store between 59-86f

Avoid frddzing and excessive heat.

Inactive ingredients

Aqua(water),Carbomer,Triethanolamine.